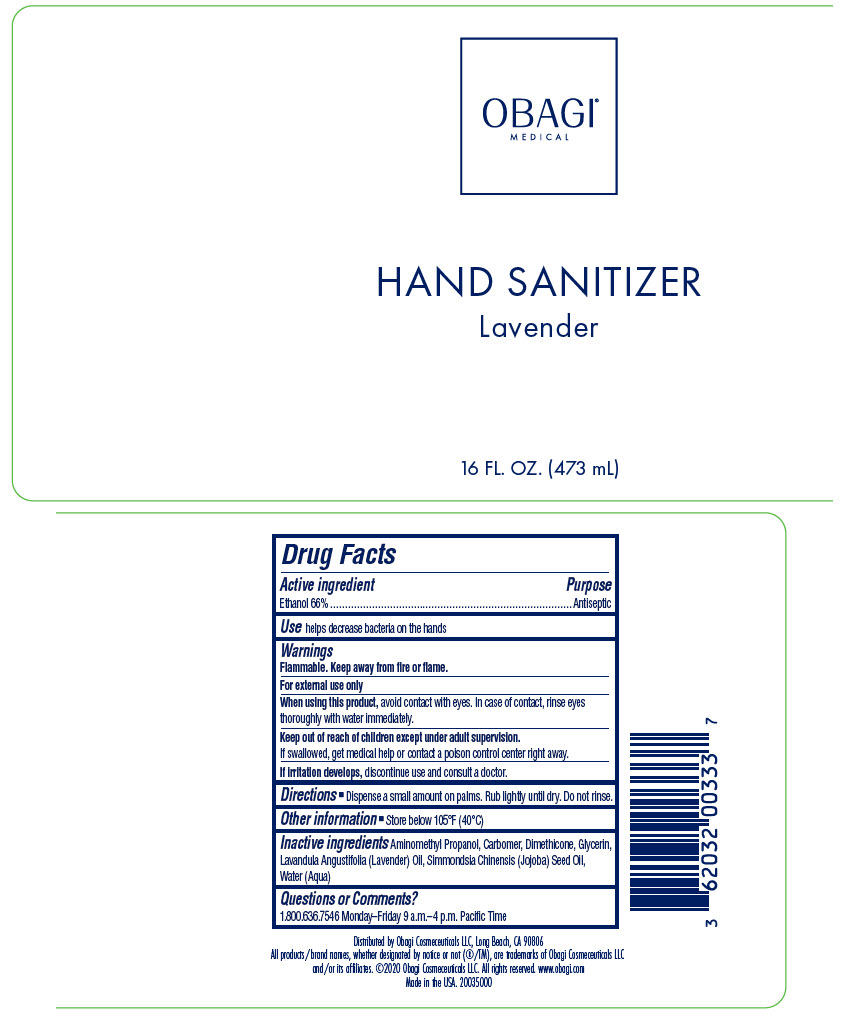 DRUG LABEL: OBAGI MEDICAL HAND SANITIZER LAVENDER
NDC: 62032-004 | Form: GEL
Manufacturer: OBAGI COSMECEUTICALS LLC
Category: otc | Type: HUMAN OTC DRUG LABEL
Date: 20200625

ACTIVE INGREDIENTS: ALCOHOL 66 mL/100 mL
INACTIVE INGREDIENTS: AMINOMETHYLPROPANOL; CARBOMER HOMOPOLYMER, UNSPECIFIED TYPE; DIMETHICONE; GLYCERIN; LAVENDER OIL; JOJOBA OIL; WATER

OBAGI® MEDICAL HAND SANITIZER LAVENDER

Drug Facts

Active ingredient

Ethanol 66%

Purpose

Antiseptic

Use

helps decrease bacteria on the hands

Warnings

Flammable. Keep away from fire or flame.

For external use only

When using this product, avoid contact with eyes. In case of contact, rinse eyes thoroughly with water immediately.

Keep out of reach of children except under adult supervision.

If swallowed, get medical help or contact a poison control center right away.

STOP USE

If irritation develops, discontinue use and consult a doctor.

Directions

- Dispense a small amount on palms. Rub lightly until dry. Do not rinse.

Other information

- Store below 105°F (40°C)

Inactive ingredients

Aminomethyl Propanol, Carbomer, Dimethicone, Glycerin, Lavandula Angustifolia (Lavender) Oil, Simmondsia Chinensis (Jojoba) Seed Oil, Water (Aqua)

Questions or Comments?

1.800.636.7546 Monday–Friday 9 a.m.–4 p.m. Pacific Time

Distributed by Obagi Cosmeceuticals LLC, Long Beach, CA 90806

PRINCIPAL DISPLAY PANEL - 473 mL Bottle Label

OBAGI®
MEDICAL

HAND SANITIZER
Lavender

16 FL. OZ. (473 mL)